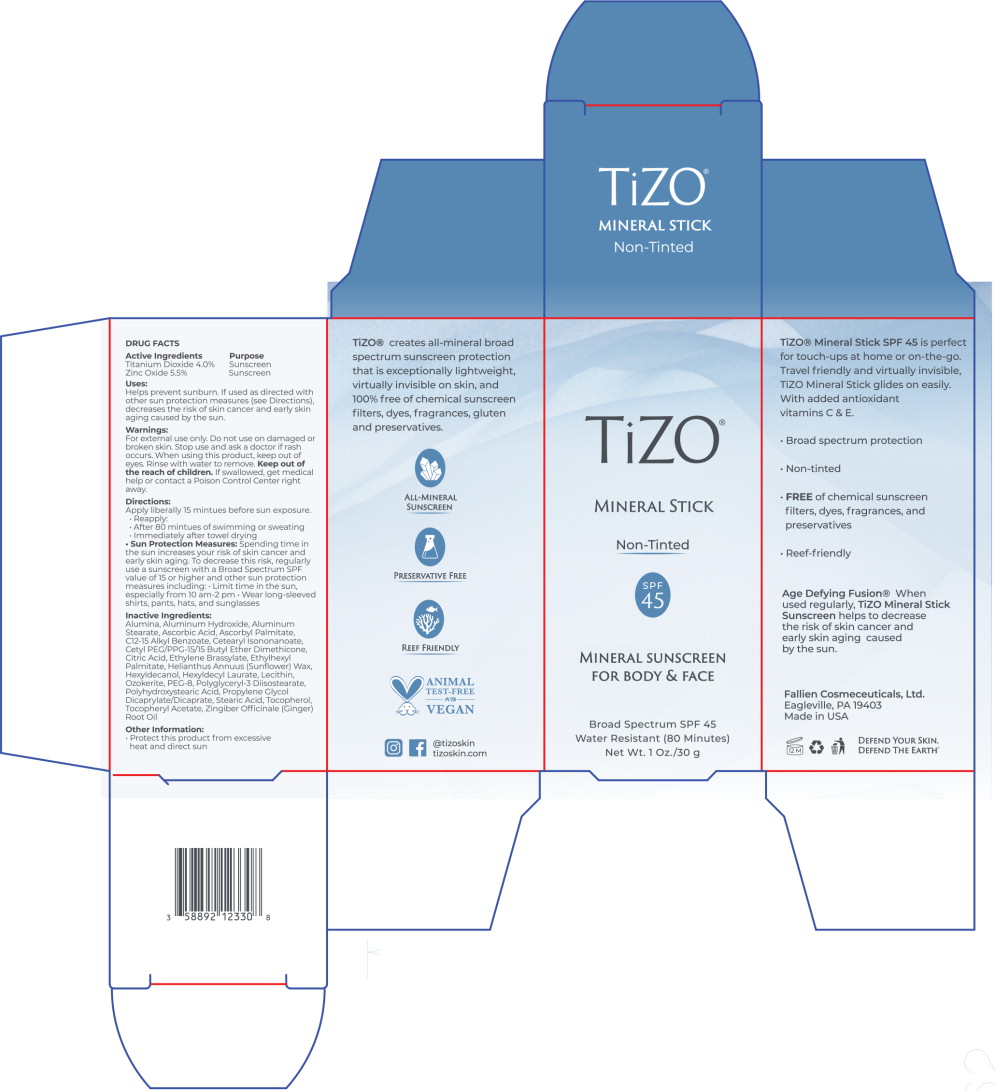 DRUG LABEL: TiZO Mineral Stick Non-Tinted SPF 45
NDC: 58892-123 | Form: STICK
Manufacturer: Fallien Cosmeceuticals, LTD
Category: otc | Type: HUMAN OTC DRUG LABEL
Date: 20241025

ACTIVE INGREDIENTS: TITANIUM DIOXIDE 40 mg/1 g; ZINC OXIDE 55 mg/1 g
INACTIVE INGREDIENTS: ALUMINUM OXIDE; ALUMINUM HYDROXIDE; ALUMINUM STEARATE; ASCORBIC ACID; ASCORBYL PALMITATE; ALKYL (C12-15) BENZOATE; CETEARYL ISONONANOATE; CETYL PEG/PPG-10/1 DIMETHICONE (HLB 4); CITRIC ACID MONOHYDRATE; ETHYLENE BRASSYLATE; DIPROPYLENE GLYCOL CAPRYLATE; ETHYLHEXYL PALMITATE; HELIANTHUS ANNUUS SEED WAX; HEXYLDECANOL; HEXYL LAURATE; LECITHIN, SUNFLOWER; CERESIN; POLYETHYLENE GLYCOL 400; POLYGLYCERYL-3 DIISOSTEARATE; POLYHYDROXYSTEARIC ACID (2300 MW); STEARIC ACID; TOCOPHEROL; .ALPHA.-TOCOPHEROL ACETATE; GINGER OIL

DRUG FACTS

Active Ingredients:

Titanium Dioxide 4.0%

Zinc Oxide 5.5%

Purpose:

Sunscreen

Sunscreen

Uses:

Helps prevent sunburn. If used as directed with other sun protection measures (see Directions), decreases the risk of skin cancer and early skin aging caused by the sun.

Warnings:

For external use only. Do not use on damaged or broken skin.

Stop use and ask a doctor if rash occurs.

When using this product, keep out of eyes. Rinse with water to remove.

KEEP OUT OF REACH OF CHILDREN

Keep out of the reach of children.If swallowed, get medical help or contact a Poison Control Center right away.

Directions:

Apply liberally 15 minutes before sun exposure.

- Reapply:
- After 80 minutes of swimming or sweating
- Immediately after towel drying
- Sun Protection Measures:Spending time in the sun increases your risk of skin cancer and early skin aging. To decrease this risk, regularly use a sunscreen with a Broad Spectrum SPF value of 15 or higher and other sun protection measures including:
- Limit time in the sun, especially from 10 am-2 pm
- Wear long-sleeved shirts, pants, hats, and sunglasses

Inactive Ingredients:

Alumina, Aluminum Hydroxide, Aluminum Stearate, Ascorbic Acid, Ascorbyl Palmitate, C12-15 Alkyl Benzoate, Cetearyl Isononanoate, Cetyl PEG/PPG-15/15 Butyl Ether Dimethicone, Citric Acid, Ethylene Brassylate, EthylhexI Palmitate, Helianthus Annuus (Sunflower) Wax, Hexyldecanol, Hexyldecyl Laurate, Lecithin, Ozokerite, PEG-8, Polyglyceryl-3 Diisostearate, Polyhydroxystearic Acid, Propylene Glycol Dicaprylate/Dicaprate, Stearic Acid, Tocopherol, Tocopheryl Acetate, Zingiber Officinale (Ginger) Root Oil

Other Information:

- Protect this product from excessive heat and direct sun

Keep out of the reach of children.

Principal Display Panel – 30 g Carton Label

TiZO®

MINERAL STICK

Non-Tinted

MINERAL SUNSCREEN
FOR BODY & FACE

Broad Spectrum SPF 45

Water Resistant (80 Minutes)

Net Wt. 1 Oz./30 g